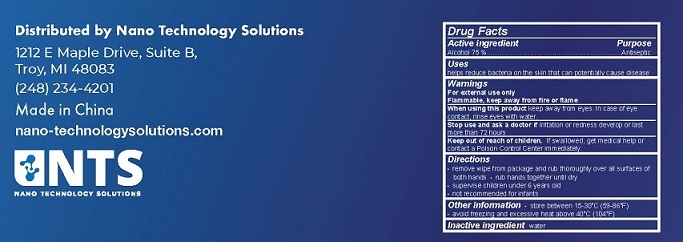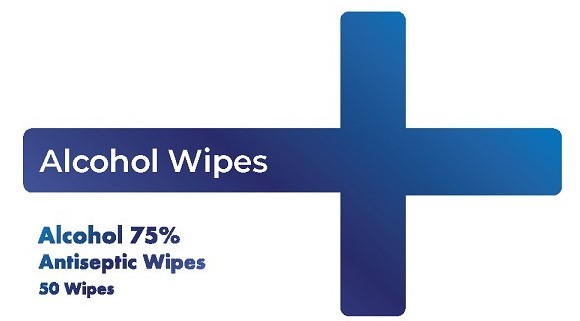 DRUG LABEL: NTS Alcohol Wipes
NDC: 76537-004 | Form: CLOTH
Manufacturer: Nano Technology Solutions
Category: otc | Type: HUMAN OTC DRUG LABEL
Date: 20200607

ACTIVE INGREDIENTS: ALCOHOL 75 mL/100 mL
INACTIVE INGREDIENTS: WATER

NTS Alcohol Wipes

Drug Facts

Active ingredient

Alcohol 75%

Purpose
Antiseptic

Uses

helps reduce bacteria on the skin that can potentially cause disease

Warnings
For external use only.
Flammable. Keep away from fire or flame.

When using this product keep away from eyes. In case of eye contact, rinse eyes with water.

Stop use and ask a doctor if irritation or redness develop or last more than 72 hours.

Keep out of reach of children. If swallowed, get medical help or contact a Poison Control Center immediately.

Directions

- remove wipe from package and rub thoroughly over all surfaces of both hands
- rub hands together until dry
- supervise children under 6 years old
- not recommended for infants

Other information

- store between 15-30°C (59-86°F)
- avoid freezing and excessive heat above 40°C (104°F)

Inactive ingredient water

Distributed by Nano Technology Solutions

1212 Maple Drive, Suite B

Troy, MI 48083

(248) 234-4201

Made in China

nano-technologysolutions.com

PACKAGE LABEL

Alcohol Wipes
Alcohol 75%
Antiseptic Wipes
50 Wipes